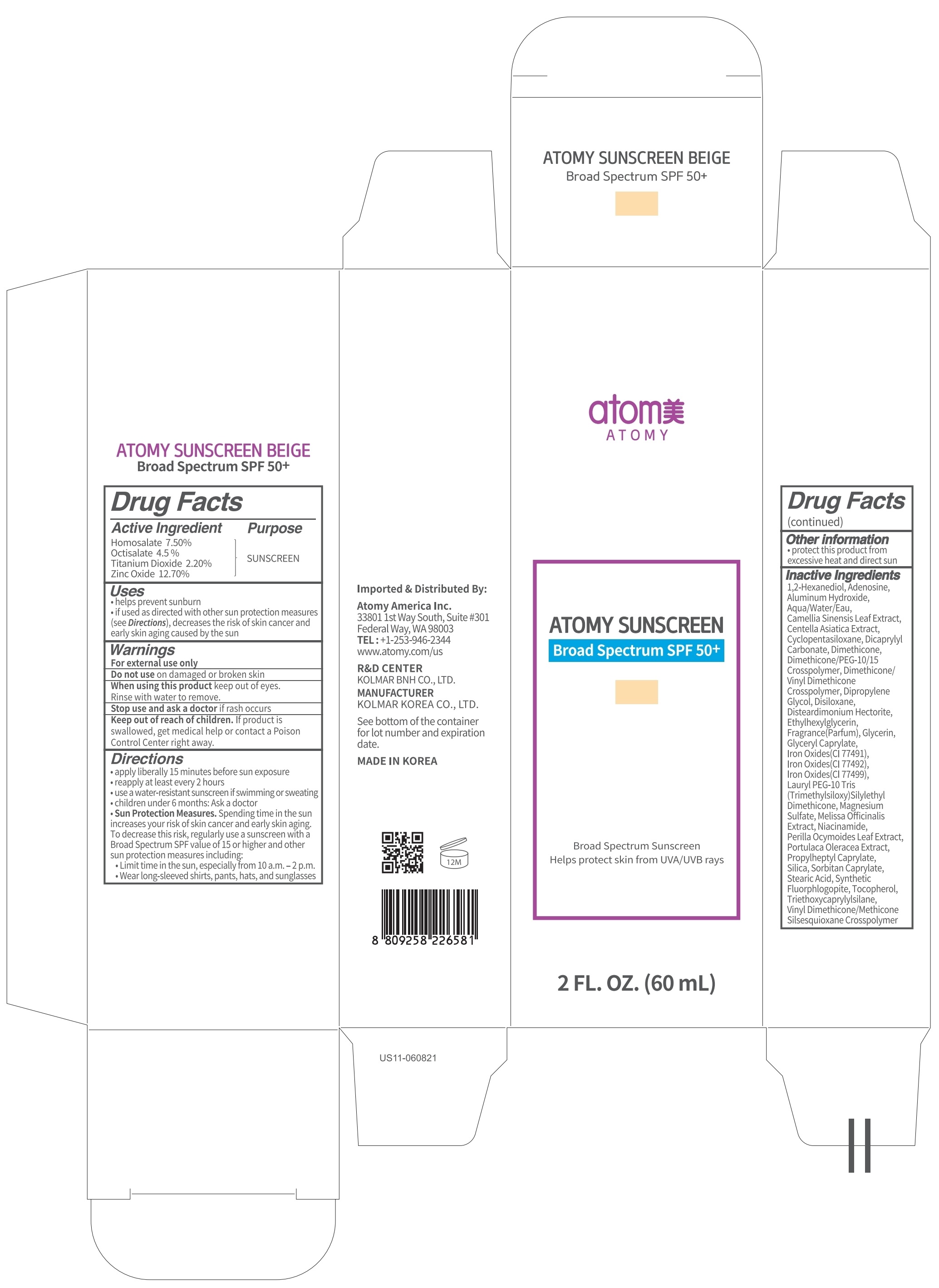 DRUG LABEL: Atomy Sunscreen Beige Broad Spectrum SPF 50 PLUS
NDC: 52257-1420 | Form: CREAM
Manufacturer: ATOMY CO., LTD.
Category: otc | Type: HUMAN OTC DRUG LABEL
Date: 20241202

ACTIVE INGREDIENTS: HOMOSALATE 4.5 g/60 mL; OCTISALATE 2.7 g/60 mL; TITANIUM DIOXIDE 1.32 g/60 mL; ZINC OXIDE 7.62 g/60 mL
INACTIVE INGREDIENTS: WATER; CYCLOMETHICONE 5; DIPROPYLENE GLYCOL

ACTIVE INGREDIENTS

HOMOSALATE 7.50%
OCTISALATE 4.50%
TITANIUM DIOXIDE 2.20%
ZINC OXIDE 12.70%

INACTIVE INGREDIENTS

Aqua/Water/Eau, Cyclopentasiloxane, Dipropylene Glycol, Disiloxane, Lauryl Peg-10 Tris(Trimethylsiloxy)Silylethyl Dimethicone, Glycerin, Niacinamide, Propylheptyl Caprylate, Portulaca Oleracea Extract, Silica, Dimethicone, Disteardimonium Hectorite, Magnesium Sulfate, Dicaprylyl Carbonate, 1,2-Hexanediol, Vinyl Dimethicone/Methicone Silsesquioxane Crosspolymer, Synthetic Fluorphlogopite, Triethoxycaprylylsilane, Aluminum Hydroxide, Stearic Acid, Sorbitan Caprylate, Dimethicone/Peg-10/15 Crosspolymer, Fragrance(Parfum), Iron Oxides(CI 77492), Dimethicone/Vinyl Dimethicone Crosspolymer, Glyceryl Caprylate, Ethylhexylglycerin, Adenosine, Iron Oxides(CI 77491), Iron Oxides(CI 77499), Tocopherol, Camellia Sinensis Leaf Extract, Melissa Officinalis Extract, Centella Asiatica Extract, Perilla Ocymoides Leaf Extract

PURPOSE

Sunscreen

WARNINGS

For external use only
Do not useon damaged or broken skin
When using this productkeep out of eyes. Rinse with water to remove.
Stop use and ask a doctorif rash occurs
Keep out of reach of children. If product is swallowed, get medical help or contact a Poison Control Center right away.

Keep out of reach of children. If product is swallowed, get medical help or contact a Poison Control Center right away.

Uses:

• Helps prevent sunburn
• If used as directed with other sun protection measures
(see Directions), decreases the risk of skin cancer and early skin aging caused by the sun

Other Information:
Protect this product from excessive heat and direct sun

Directions:

• Apply liberally 15 minutes before sun exposure
• Reapply at least every 2 hours
• Use a water-resistant sunscreen if swimming or sweating
• Children under 6 months: Ask a doctor
• Sun Protection Measures. Spending time in the sun increases your risk of skin cancer and early skin aging.
To decrease this risk, regularly use a sunscreen with a Broad Spectrum SPF value of 15 or higher and other sun protection measures including:
• Limit time in the sun, especially from 10 a.m. ‒ 2 p.m.
• Wear long-sleeved shirts, pants, hats, and sunglasses